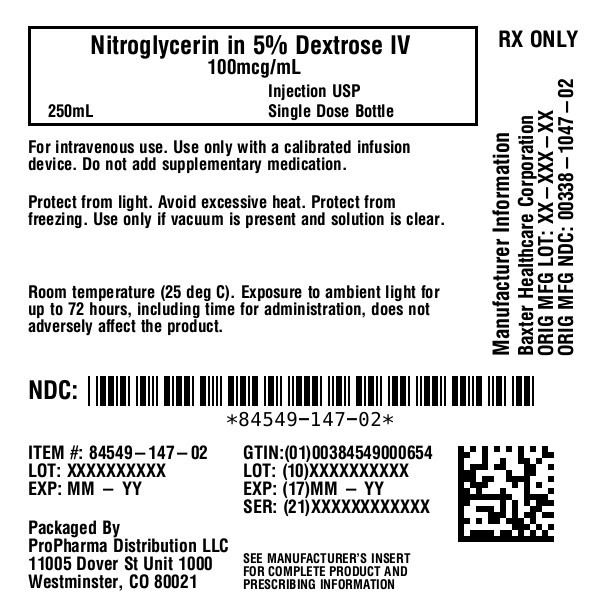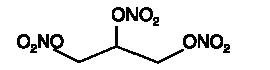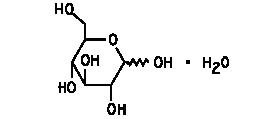 DRUG LABEL: Nitroglycerin In Dextrose
NDC: 84549-147 | Form: INJECTION
Manufacturer: ProPharma Distribution
Category: prescription | Type: HUMAN PRESCRIPTION DRUG LABEL
Date: 20251218

ACTIVE INGREDIENTS: NITROGLYCERIN 10 mg/100 mL
INACTIVE INGREDIENTS: DEXTROSE MONOHYDRATE 5 g/100 mL; ALCOHOL 0.84 mL/100 mL; CITRIC ACID MONOHYDRATE 105 mg/100 mL; SODIUM HYDROXIDE; WATER; HYDROCHLORIC ACID; PROPYLENE GLYCOL

Nitroglycerin in 5% Dextrose Injection
For intravenous use only

DESCRIPTION

Nitroglycerin is 1,2,3-propanetriol trinitrate, an organic nitrate whose structural formula is

whose empiric formula is C3H5N3O9, and whose molecular weight is 227.09. The organic nitrates are vasodilators, active on both arteries and veins.

Dextrose (Dextrose Hydrous, USP) is D-glucose monohydrate, a hexose sugar whose structural formula is

whose empiric formula is C6H12O6• H2O, and whose molecular weight is 198.17.

Dextrose is derived from corn.

Nitroglycerin in 5% Dextrose Injection is a sterile, nonpyrogenic solution of nitroglycerin and dextrose in water for injection. The solution is clear and practically colorless. Each 100 mL contains 10 mg, 20 mg, or 40 mg nitroglycerin (added as Diluted Nitroglycerin, USP with propylene glycol); 5 g Dextrose Hydrous, USP; 0.84 mL Alcohol, USP (added as a dissolution aid); and 105 mg Citric Acid Hydrous, USP (added as a buffer). The pH of the solution is adjusted with sodium hydroxide and, if necessary, hydrochloric acid.

Although dry nitroglycerin is explosive, nitroglycerin in 5% dextrose is not.

Composition, osmolarity and pH are given in Table 1.

Table 1 | Composition |  | [Normal physiologic osmolarity range is approximately 280 to 310 mOsmol/L. Administration of substantially hypertonic solutions (≥600 mOsmol/L) may cause vein damage.] Osmolarity (mOsmol/L) (calc) | pH
Table 1 | Nitroglycerin (mcg/mL) | Dextrose Hydrous, USP (g/L) | [Normal physiologic osmolarity range is approximately 280 to 310 mOsmol/L. Administration of substantially hypertonic solutions (≥600 mOsmol/L) may cause vein damage.] Osmolarity (mOsmol/L) (calc) | pH
25 mg Nitroglycerin in 5% Dextrose Injection | 100 | 50 | 428 | 4.0; (3.0 to 5.0)
50 mg Nitroglycerin in 5% Dextrose Injection | 200 | 50 | 440 | 4.0; (3.0 to 5.0)
100 mg Nitroglycerin in 5% Dextrose Injection | 400 | 50 | 465 | 4.0; (3.0 to 5.0)

CLINICAL PHARMACOLOGY

The principal pharmacological action of nitroglycerin is relaxation of vascular smooth muscle and consequent dilatation of peripheral arteries and veins, especially the latter. Dilatation of the veins promotes peripheral pooling of blood and decreases venous return to the heart, thereby reducing left ventricular end-diastolic pressure and pulmonary capillary wedge pressure (preload). Arteriolar relaxation reduces systemic vascular resistance, systolic arterial pressure, and mean arterial pressure (afterload). Dilatation of the coronary arteries also occurs. The relative importance of preload reduction, afterload reduction, and coronary dilatation remains undefined.

Dosing regimens for most chronically used drugs are designed to provide plasma concentrations that are continuously greater than a minimally effective concentration. This strategy is inappropriate for organic nitrates. Several well-controlled clinical trials have used exercise testing to assess the anti-anginal efficacy of continuously-delivered nitrates. In the large majority of these trials, active agents were indistinguishable from placebo after 24 hours (or less) of continuous therapy. Attempts to overcome nitrate tolerance by dose escalation, even to doses far in excess of those used acutely, have consistently failed. Only after nitrates have been absent from the body for several hours has their anti-anginal efficacy been restored.

Pharmacokinetics:

The volume of distribution of nitroglycerin is about 3 L/kg, and nitroglycerin is cleared from this volume at extremely rapid rates, with a resulting serum half-life of about 3 minutes. The observed clearance rates (close to 1 L/kg/min) greatly exceed hepatic blood flow; known sites of extrahepatic metabolism include red blood cells and vascular walls.

The first products in the metabolism of nitroglycerin are inorganic nitrate and the 1,2-and 1,3- dinitroglycerols. The dinitrates are less effective vasodilators than nitroglycerin, but they are longer-lived in the serum, and their net contribution to the overall effect of chronic nitroglycerin regimens is not known. The dinitrates are further metabolized to (non-vasoactive) mononitrates and, ultimately, to glycerol and carbon dioxide.

To avoid development of tolerance to nitroglycerin, drug-free intervals of 10-12 hours are known to be sufficient; shorter intervals have not been well studied. In one well-controlled clinical trial, subjects receiving nitroglycerin appeared to exhibit a rebound or withdrawal effect, so that their exercise tolerance at the end of the daily drug-free interval was lessthan that exhibited by the parallel group receiving placebo.

Clinical Trials:

Blinded, placebo-controlled trials of intravenous nitroglycerin have not been reported, but multiple investigators have reported open-label studies, and there are scattered reports of studies in which intravenous nitroglycerin was tested in blinded fashion against sodium nitroprusside.

In each of these studies, therapeutic doses of intravenous nitroglycerin were found to reduce systolic and diastolic arterial blood pressure. The heart rate was usually increased, presumably as a reflexive response to the fall in blood pressure. Coronary perfusion pressure was usually, but not always, maintained.

Intravenous nitroglycerin reduced central venous pressure (CVP), right atrial pressure (RAP), pulmonary arterial pressure (PAP), pulmonary-capillary wedge pressure (PCWP), pulmonary vascular resistance (PVR), and systemic vascular resistance (SVR). When these parameters were elevated, reducing them toward normal usually caused a rise in cardiac output. Conversely, intravenous nitroglycerin usually reducedcardiac output when it was given to patients whose CVP, RAP, PAP, PCWP, PVR, and SVR were all normal.

Most clinical trials of intravenous nitroglycerin have been brief; they have typically followed hemodynamic parameters during a single surgical procedure. In one careful study, one of the few that lasted more than a few hours, continuous intravenous nitroglycerin had lost almost all of its hemodynamic effect after 48 hours. In the same study, patients who received nitroglycerin infusions for only 12 hours out of each 24 demonstrated no similar attenuation of effect. These results are consistent with those seen in multiple large, double-blind, placebo-controlled trials of other formulations of nitroglycerin and other nitrates.

INDICATIONS AND USAGE

Nitroglycerin in 5% Dextrose Injection is indicated for treatment of peri-operative hypertension; for control of heart failure in the setting of acute myocardial infarction; for treatment of angina pectoris in patients who have not responded to sublingual nitroglycerin and ß-blockers; and for induction of intraoperative hypotension.

CONTRAINDICATIONS

Nitroglycerin in 5% Dextrose Injection is contraindicated in patients who are allergic to it.

In patients with pericardial tamponade, restrictive cardiomyopathy, or constrictive pericarditis, cardiac output is dependent upon venous return. Intravenous nitroglycerin is contraindicated in patients with these conditions.

Nitroglycerin is also contraindicated in patients with increased intracranial pressure.

Do not use Nitroglycerin in 5% Dextrose Injection in patients who are taking certain drugs for erectile dysfunction (phosphodiesterase inhibitors) such as sildenafil, tadalafil, or vardenafil. Concomitant use can cause severe hypotension, syncope, or myocardial ischemia.

Do not use Nitroglycerin in 5% Dextrose Injection in patients who are taking the soluble guanylate cyclase stimulator riociguat. Concomitant use can cause hypotension.

WARNINGS

Use of PVC (polyvinyl chloride) tubing in infusion sets may lead to loss of active ingredient due to adsorption of nitroglycerin to PVC tubing, therefore dosage is affected (see Dosage and Administration). Nitroglycerin adsorption by PVC tubing is increased when the tubing is long, the flow rates are low, and the nitroglycerin concentration of the solution is high. The delivered fraction of the solution's original nitroglycerin content has been 20-60% in published studies using PVC tubing; the fraction varies with time during a single infusion, and no simple correction factor can be used. PVC tubing has been used in most published studies of intravenous nitroglycerin, but the reported doses have been calculated by simply multiplying the flow rate of the solution by the solution's original concentration of nitroglycerin. The actual doses delivered have been less, sometimes much less, than those reported.

Relatively non-adsorptive intravenous administration sets are available. If intravenous nitroglycerin is administered through non-adsorptive tubing, doses based upon published reports will generally be too high.

Some in-line intravenous filters also adsorb nitroglycerin; these filters should be avoided.

Solutions containing dextrose without electrolytes should not be administered through the same administration set as blood, as this may result in pseudoagglutination or hemolysis.

The intravenous administration of solutions may cause fluid overloading resulting in dilution of serum electrolyte concentrations, overhydration and congested states of pulmonary edema. The risk of dilutional states is inversely proportional to the electrolyte concentrations of the injections. The risk of solute overload causing congested states with peripheral and pulmonary edema is directly proportional to the electrolyte concentration of the injections.

PRECAUTIONS

Severe hypotension and shock may occur with even small doses of nitroglycerin. Monitor patients who may be volume depleted or who, for whatever reason, are already hypotensive. Hypotension induced by nitroglycerin may be accompanied by paradoxical bradycardia and increased angina pectoris.

Nitrate therapy may aggravate the angina caused by hypertrophic cardiomyopathy.

Tolerance development and occurrence of cross tolerance to other nitro compounds have been reported.

In industrial workers who have long-term exposure to unknown (presumably high) doses of organic nitrates, tolerance clearly occurs. Chest pain, acute myocardial infarction, and even sudden death have occurred during temporary withdrawal of nitrates from these workers, demonstrating the existence of true physical dependence.

Some clinical trials in angina patients have provided nitroglycerin for about 12 continuous hours of every 24-hour day. During the nitrate-free intervals in some of these trials, anginal attacks have been more easily provoked than before treatment, and patients have demonstrated hemodynamic rebound and decreasedexercise tolerance. The importance of these observations to the routine, clinical use of intravenous nitroglycerin is not known.

Lower concentrations of Nitroglycerin in 5% Dextrose Injection increase the potential precision of dosing, but these concentrations increase the total fluid volume that must be delivered to the patient. Total fluid load may be a dominant consideration in patients with compromised function of the heart, liver, and/or kidneys.

Administer nitroglycerin in 5% Dextrose Injection via an infusion pump that can maintain a constant infusion rate.

Intracoronary injection of Nitroglycerin in 5% Dextrose Injection has not been studied.

Monitor patients with known sub-clinical or overt diabetes mellitus when using solutions containing dextrose.

Laboratory Tests:

Because of the propylene glycol content of intravenous nitroglycerin, serum triglyceride assays that rely on glycerol oxidase may give falsely elevated results in patients receiving this medication.

Drug Interactions:

The vasodilating effects of nitroglycerin may be additive with those of antihypertensives (e.g., beta-blockers, calcium channel blockers and tricyclic antidepressants) and may cause increased hypotensive effects..

Concomitant use of Nitroglycerin in 5% Dextrose Injection with phosphodiesterase inhibitors (e.g. sildenafil, tadalafil, or vardenafil) can cause hypotension and is contraindicated (see Contraindications).

Concomitant use of Nitroglycerin in 5% Dextrose Injection with riociguat, a soluble guanylate cyclase stimulator, can cause hypotension and is contraindicated (see Contraindications).

Marked symptomatic orthostatic hypotension has been reported when calcium channel blockers and organic nitrates were used in combination.

Nitroglycerin at higher dosages may interfere with the anticoagulant effect of heparin. Intravenous nitroglycerin can induce heparin resistance.

Administration of Nitroglycerin in 5% Dextrose Injection through the same infusion set as blood can result in pseudoagglutination and hemolysis. Do not mix Nitroglycerin in 5% Dextrose Injection with any other medication of any kind.

Carcinogenesis, Mutagenesis, and Impairment of Fertility:

Animal carcinogenesis studies with injectable nitroglycerin have not been performed.

Rats receiving up to 434 mg/kg/day of dietary nitroglycerin for 2 years developed dose-related fibrotic and neoplastic changes in liver, including carcinomas, and interstitial cell tumors in testes. At high dose, the incidences of hepatocellular carcinomas in both sexes were 52% vs. 0% in controls and incidences of testicular tumors were 52% vs. 8% in controls. Lifetime dietary administration of up to 1058 mg/kg/day of nitroglycerin was not tumorigenic in mice.

Nitroglycerin was weakly mutagenic in Ames tests performed in two different laboratories. Nevertheless, there was no evidence of mutagenicity in an in vivodominant lethal assay with male rats treated with doses up to about 363 mg/kg/day, p.o., or in in vitrocytogenetic tests in rat and dog tissues.

In a three-generation reproduction study, rats received dietary nitroglycerin at doses up to about 434 mg/kg/day for six months prior to mating of the F0generation with treatment continuing through successive F1and F2generations. The high-dose was associated with decreased feed intake and body weight gain in both sexes at all matings. No specific effect on the fertility of the F0generation was seen. Infertility noted in subsequent generations, however, was attributed to increased interstitial cell tissue and aspermatogenesis in the high-dose males. In this three-generation study there was no clear evidence of teratogenicity.

Pregnancy:

Animal teratology studies have not been conducted with nitroglycerin injection. Teratology studies in rats and rabbits were conducted with topically applied nitroglycerin ointment at doses up to 80 mg/kg/day and 240 mg/kg/day, respectively, and no toxic effects on dams or fetuses were seen. There are no adequate and well-controlled studies in pregnant women. Nitroglycerin should be given to a pregnant woman only if clearly needed.

Nursing Mothers:

It is not known if nitroglycerin is present in human milk or if nitroglycerin has effects on milk production. The developmental and health benefits of breastfeeding should be considered along with the mother’s clinical need for nitroglycerin and any potential adverse effects on the breastfed child from nitroglycerin or from the underlying maternal condition.

Pediatric Use:

Safety and effectiveness in the pediatric population have not been established. However, the relationship between hemodynamic effects of nitroglycerin and dose in the pediatric population have been documented in the literature. Studies in the literature used doses of nitroglycerin injection in pediatric patients ranging from 0.5 to 5 mcg/kg/min. The following equation can be used to calculate the flow rate in mL/hour of nitroglycerin using the 100 mcg/mL (25 mg/250 mL) concentration of nitroglycerin.

Infusion Rate (mL/h) = [Dose (mcg/kg/min) x Weight (kg) x 60 min/h]

Final Concentration (mcg/mL)

Example calculations for infusion rates are as follows:

1. Example 1:for a 2 kg child at a dose of 0.5 µg/kg/min using a 100 mcg/mL concentration, the infusion rate would be as follows:

Infusion Rate(mL/h) = [0.5(mcg/kg/min) x 2(kg) x 60(min/h) ]= 0.6(mL/h)

100(mcg/mL)

1. Example 2:for a 10 kg child at a dose of 5 mcg/kg/min using a 100 mcg/mL concentration, the infusion rate would be as follows:

Infusion Rate(mL/h) = [5(mcg/kg/min) x 10(kg) x 60(min/h) ]= 30(mL/h)

100(mcg/mL)

Note: Very low infusion rates may require that a more dilute concentration of nitroglycerin infusion solution be prepared.

Geriatric Use:

Clinical studies of Nitroglycerin did not include sufficient numbers of subjects aged 65 and over to determine whether they respond differently from younger subjects. Other reported clinical experience has not identified differences in responses between the elderly and younger patients. In general, dose selection for an elderly patient should be cautious, usually starting at the low end of the dosing range reflecting the greater frequency of decreased hepatic, renal, or cardiac function, and of concomitant disease or other drug therapy.

Do not use unless vacuum is present and solution is clear.

ADVERSE REACTIONS

Adverse reactions to nitroglycerin are generally dose-related and almost all of these reactions are the result of nitroglycerin's activity as a vasodilator. Headache, which may be severe, is the most commonly reported side effect. Headache may be recurrent with each daily dose, especially at higher doses. Transient episodes of lightheadedness, occasionally related to blood pressure changes, may also occur. Hypotension occurs infrequently, but in some patients it may be severe enough to warrant discontinuation of therapy. Syncope, crescendo angina, and rebound hypertension have been reported but are uncommon.

Allergic reactions to nitroglycerin are also uncommon, and the great majority of those reported have been cases of contact dermatitis or fixed drug eruptions in patients receiving nitroglycerin in ointments or patches. There have been a few reports of genuine anaphylactoid reactions, and these reactions can probably occur in patients receiving nitroglycerin by any route.

Extremely rarely, ordinary doses of organic nitrates have caused methemoglobinemia in normal-seeming patients. Methemoglobinemia is so infrequent at these doses that further discussion of its diagnosis and treatment is deferred (see Overdosage).

Dyspnea has also been reported.

Data are not available to allow estimation of the frequency of adverse reactions during treatment with Nitroglycerin in 5% Dextrose Injection.

OVERDOSAGE

Signs and symptoms of overdose are generally similar to the described adverse reactions (see Adverse Reactions).

There is no specific antidote for overdose of nitroglycerin. The risk of overdose can be minimized by close monitoring during treatment.

Hemodynamic Effects:

The ill effects of nitroglycerin overdose are generally the results of nitroglycerin's capacity to induce vasodilation, venous pooling, reduced cardiac output, and hypotension. These hemodynamic changes may have protean manifestations, including increased intracranial pressure, with any or all of persistent throbbing headache, confusion, and moderate fever; vertigo; palpitations; visual disturbances; nausea and vomiting (possibly with colic and even bloody diarrhea); syncope (especially in the upright posture); air hunger and dyspnea, later followed by reduced ventilatory effort; diaphoresis, with the skin either flushed or cold and clammy; heart block and bradycardia; paralysis; coma; seizures; and death.

Laboratory determinations of serum levels of nitroglycerin and its metabolites are not widely available, and such determinations have, in any event, no established role in the management of nitroglycerin overdose.

No data are available to suggest physiological maneuvers (e.g., maneuvers to change the pH of the urine) that might accelerate elimination of nitroglycerin and its active metabolites. Similarly, it is not known which -if any- of these substances can usefully be removed from the body by hemodialysis.

No specific antagonist to the vasodilator effects of nitroglycerin is known, and no intervention has been subject to controlled study as a therapy of nitroglycerin overdose. Because the hypotension associated with nitroglycerin overdose is the result of venodilatation and arterial hypovolemia, prudent therapy in this situation should be directed toward increase in central fluid volume. Passive elevation of the patient's legs may be sufficient, but intravenous infusion of normal saline or similar fluid may also be necessary.

The use of epinephrine or other arterial vasoconstrictors in this setting is likely to do more harm than good.

In patients with renal disease or heart failure, therapy resulting in central volume expansion is not without hazard. Treatment of nitroglycerin overdose in these patients may be subtle and difficult, and invasive monitoring may be required.

Methemoglobinemia:

Nitrate ions liberated during metabolism of nitroglycerin can oxidize hemoglobin into methemoglobin. Even in patients totally without cytochrome b5reductase activity, however, and even assuming that the nitrate moieties of nitroglycerin are quantitatively applied to oxidation of hemoglobin, about 1 mg/kg of nitroglycerin should be required before any of these patients manifests clinically significant (≥ 10%) methemoglobinemia. In patients with normal reductase function, significant production of methemoglobin should require even larger doses of nitroglycerin. In one study in which 36 patients received 2-4 weeks of continuous nitroglycerin therapy at 3.1 to 4.4 mg/hr, the average methemoglobin level measured was 0.2%; this was comparable to that observed in parallel patients who received placebo.

Cases of methemoglobinemia have been reported with moderate doses of organic nitrates.

Methemoglobin levels are available from most clinical laboratories. The diagnosis should be suspected in patients who exhibit signs of impaired oxygen delivery despite adequate cardiac output and adequate arterial pO2. Classically, methemoglobinemic blood is described as chocolate brown, without color change on exposure to air.

When methemoglobinemia is diagnosed, discontinue treatment of nitroglycerin. If condition is not reversed, treat with methylene blue, 1-2 mg/kg intravenously.

DOSAGE AND ADMINISTRATION

Nitroglycerin in 5% Dextrose Injection is intended for intravenous administration using sterile equipment. Administer Nitroglycerin in 5% Dextrose Injection only via an infusion pump that can maintain a constant infusion rate. Do not use a container which has lost its vacuum, or one in which particulate matter is visible.

Dosage is affected by the type of infusion set used (see Warnings). Although the usual adult starting dose in published studies has been 25 mcg/min or more, these studies used PVC tubing, so the delivered doses were less than those reported. When nonadsorptive tubing is used, doses must be reduced(see Warningsand Precautions).

The dosage must be determined by the patient’s individual requirement and depending on the required response and possible adverse effects (see Adverse Reactions).

Even using nonadsorptive tubing, the dose necessary to achieve a given response will vary greatly from patient to patient. Patients with normal or low left-ventricular filling pressure (e.g., patients with uncomplicated angina pectoris) may respond fully to as little as 5 mcg/min, while other patients may require a dose that is one or even two orders of magnitude higher. Continuous monitoring of blood pressure and heart rate is necessary in all patients receiving this medication; in many cases, invasive monitoring of pulmonary capillary wedge pressure will also be indicated.

Lower concentrations of Nitroglycerin in 5% Dextrose Injection increase the potential precision of dosing, but these concentrations increase the total fluid volume that must be delivered to the patient. Total fluid load may be a dominant consideration in patients with compromised function of the heart, liver, and/or kidneys. The necessary flow rates to achieve various dose rates with the available concentrations are shown in the following table.

Using nonadsorptive tubing, the initial adult dosage of Nitroglycerin in 5% Dextrose Injection should be 5 mcg/min. Subsequent titration must be guided by the clinical results, with dose increments becoming more cautious as partial response is seen. Initial titration should be in 5 mcg/min increments at intervals of 3 to 5 minutes. If no response is seen at 20 mcg/min, increments of 10 and even 20 mcg/min can be used. Once some hemodynamic response is observed, dosage increments should be smaller and less frequent.

When the concentration is changed, the tubing must be disconnected from the patient and flushed with the new solution before therapy is continued. If this precaution is not taken, then depending upon the tubing, pump, and flow rate used, it might be several hours before nitroglycerin is delivered at the desired rate.

Parenteral drug products should be inspected visually for particulate matter and discoloration prior to administration, whenever solution and container permit. Do not administer unless the solution is clear and the seal is intact.

Do not add supplementary medication to Nitroglycerin in 5% Dextrose Injection.

Infusion Rate (mL/h) = [Dose (mcg/min) x 60 min/h]

Concentration (mcg/mL)

Example calculations for infusion rates are as follows:

1. Example 1:for a dose of 30 µg/min using a 100 mcg/mL concentration, the infusion rate would be as follows:

Infusion Rate(mL/h) = [30 (mcg/min) x 60 (min/h) ]= 18(mL/h)

100(mcg/mL)

1. Example 2:for a dose of 240 mcg/min using a 400 mcg/mL concentration, the infusion rate would be as follows:

Infusion Rate(mL/h) = [5 (mcg/min) x 60 (min/h) ]= 36(mL/h)

400(mcg/mL)

HOW SUPPLIED

Nitroglycerin in 5% Dextrose Injection is supplied in glass container as follows:

 | Size (mL) | NDC | Product Name
 | 250 | 84549-147-02 | 25 mg Nitroglycerin in 5% Dextrose Injection

Minimize exposure of pharmaceutical products to heat. Avoid excessive heat. Protect from freezing. Store the product at room temperature (25°C). Brief exposure up to 40°C does not adversely affect the product. Protect from light until time of use.Discard any unused portion.